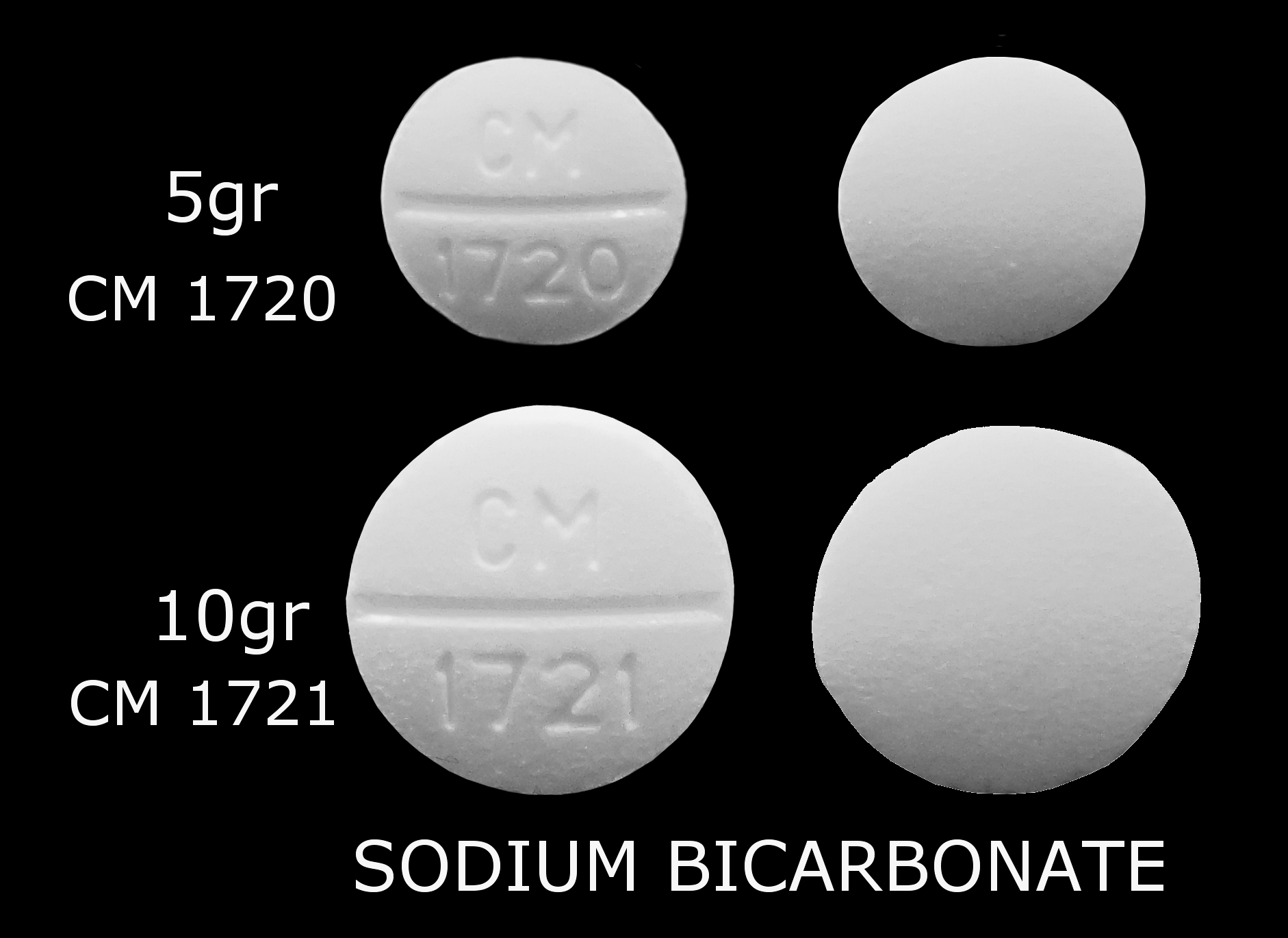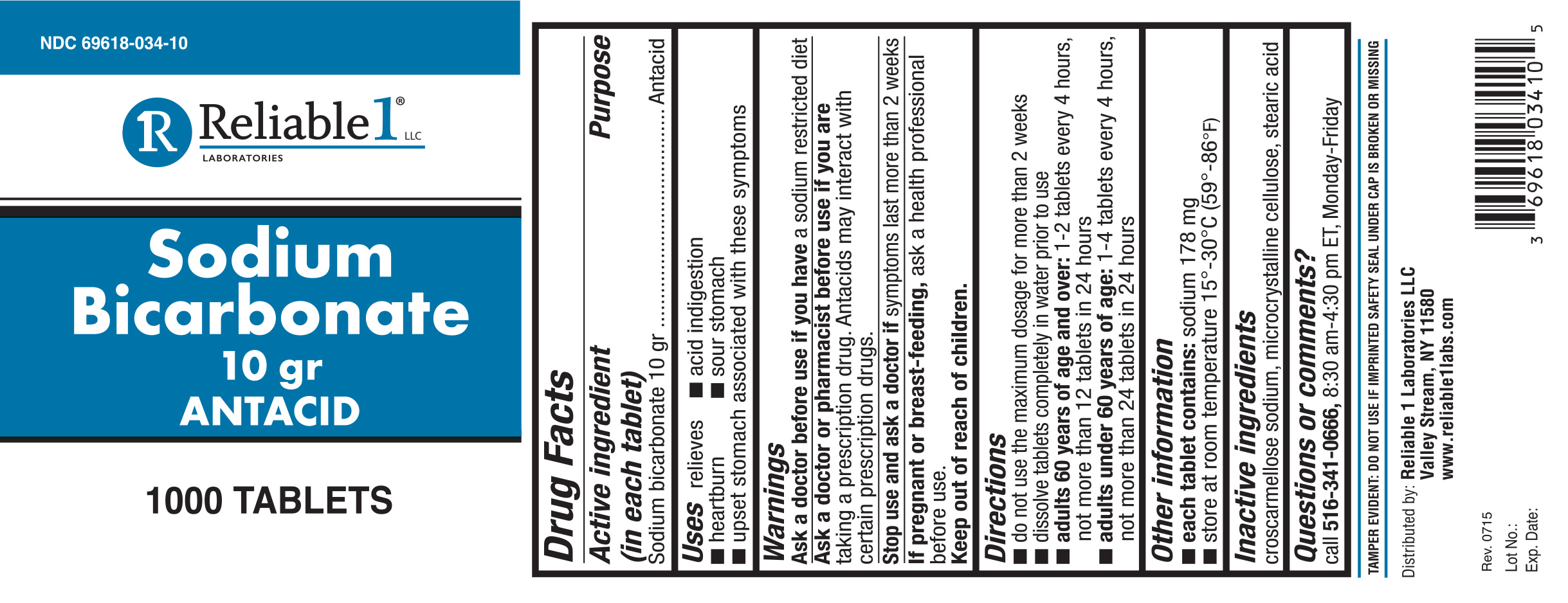 DRUG LABEL: Sodium Bicarbonate 10 gr
NDC: 69618-034 | Form: TABLET, SOLUBLE
Manufacturer: Reliable 1 Laboratories LLC
Category: otc | Type: HUMAN OTC DRUG LABEL
Date: 20250115

ACTIVE INGREDIENTS: SODIUM BICARBONATE 648 mg/1 1
INACTIVE INGREDIENTS: CELLULOSE, MICROCRYSTALLINE; STEARIC ACID; CROSCARMELLOSE SODIUM

Sodium Bicarbonate 10 gr

Active ingredient (in each tablet)

Sodium bicarbonte 10 gr

Purpose

Antacid

INDICATIONS AND USAGE

Uses relieves

- acid indigestion
- heartburn
- sour stomach
- upset stomach associated with these symptoms

Warnings

Ask a doctor before use if you have a sodium restricted diet

Ask a doctor or pharmacist before use if you are taking a prescription drug. Antacids may interact with certain prescription drugs.

Stop use and ask a doctor if symptoms last more than 2 weeks

If pregnant or breast-feeding, ask a health professional before use.

Keep out of reach of children.

Ask a doctor before use if you have a sodium restricted diet

Ask a doctor or pharmacist before use if you are taking a prescription drug. Antacids may interact with certain prescription drugs.

Stop use and ask a doctor if symptoms last more than 2 weeks

PREGNANCY OR BREAST FEEDING

If pregnant or breast-feeding, ask a health professional before use.

keep out of reach of children

Directions

- do not use the maximum dosage for more than 2 weeks
- dissolve tablets completely in water prior to use
- adults 60 years of age and over: 1-2 tablets every 4 hours, not more than 12 tabelts in 24 hours
- adults under 60 years of age: 1-4 tablets every 4 hours, not more than 24 tablets in 24 hours

Inactive ingredients

croscarmellose sodium, microcrystalline cellulose, stearic acid

Questions or comments?

call 516-341-0666, 8:30 am- 4:30 pm ET, Monday-Friday

TAMPER EVIDENT: DO NOT USE IF IMPRINTED SAFTY SEAL UNDER CAP IS BROKEN OR MISSING

Distributed by: Reliable 1 Laboratories LLC

Valley Stream, NY 11580

www.reliable1labs.com

PACKAGE LABEL

NDC 69618-034-10

Sodium Bicarbonate

10 gr

ANTACID

1000 TABLETS